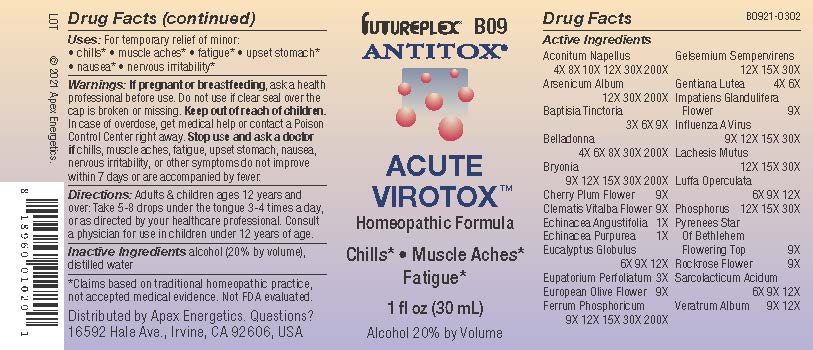 DRUG LABEL: B09
NDC: 63479-0209 | Form: SOLUTION/ DROPS
Manufacturer: Apex Energetics Inc.
Category: homeopathic | Type: HUMAN OTC DRUG LABEL
Date: 20240108

ACTIVE INGREDIENTS: ECHINACEA ANGUSTIFOLIA 1 [hp_X]/1 mL; ACONITUM NAPELLUS 200 [hp_X]/1 mL; PRUNUS CERASIFERA FLOWER 9 [hp_X]/1 mL; PHOSPHORUS 30 [hp_X]/1 mL; HELIANTHEMUM NUMMULARIUM FLOWER 9 [hp_X]/1 mL; BAPTISIA TINCTORIA ROOT 9 [hp_X]/1 mL; CLEMATIS VITALBA FLOWER 9 [hp_X]/1 mL; EUCALYPTUS GLOBULUS LEAF 12 [hp_X]/1 mL; BRYONIA ALBA ROOT 200 [hp_X]/1 mL; FERROSOFERRIC PHOSPHATE 200 [hp_X]/1 mL; ATROPA BELLADONNA 200 [hp_X]/1 mL; ARSENIC TRIOXIDE 200 [hp_X]/1 mL; GELSEMIUM SEMPERVIRENS ROOT 30 [hp_X]/1 mL; GENTIANA LUTEA ROOT 6 [hp_X]/1 mL; IMPATIENS GLANDULIFERA FLOWER 9 [hp_X]/1 mL; LACHESIS MUTA VENOM 30 [hp_X]/1 mL; LACTIC ACID, L- 12 [hp_X]/1 mL; VERATRUM ALBUM ROOT 12 [hp_X]/1 mL; EUPATORIUM PERFOLIATUM FLOWERING TOP 3 [hp_X]/1 mL; OLEA EUROPAEA FLOWER 9 [hp_X]/1 mL; INFLUENZA A VIRUS WHOLE 30 [hp_X]/1 mL; LUFFA OPERCULATA FRUIT 12 [hp_X]/1 mL; ECHINACEA PURPUREA 1 [hp_X]/1 mL; ORNITHOGALUM UMBELLATUM FLOWERING TOP 9 [hp_X]/1 mL
INACTIVE INGREDIENTS: WATER; ALCOHOL

B09

Active Ingredients
Aconitum Napellus | 4X 8X 10X 12X 30X 200X
Arsenicum Album | 12X 30X 200X
Baptisia Tinctoria | 3X 6X 9X
Belladonna | 4X 6X 8X 30X 200X
Bryonia | 9X 12X 15X 30X 200X
Cherry Plum Flower | 9X
Clematis Vitalba Flower | 9X
Echinacea Angustifolia | 1X
Echinacea Purpurea | 1X
Eucalyptus Globulus | 6X 9X 12X
Eupatorium Perfoliatum | 3X
European Olive Flower | 9X
Ferrum Phosphoricum | 9X 12X 15X 30X 200X
Gelsemium Sempervirens | 12X 15X 30X
Gentiana Lutea | 4X 6X
Impatiens Glandulifera Flower | 9X
Influenza A Virus | 9X 12X 15X 30X
Lachesis Mutus | 12X 15X 30X
Luffa Operculata | 6X 9X 12X
Phosphorus | 12X 15X 30X
Pyrenees Star Of Bethlehem Flowering Top | 9X
Rockrose Flower | 9X
Sarcolacticum Acidum | 6X 9X 12X
Veratrum Album | 9X 12X

INDICATIONS AND USAGE

Uses:

For temporary relief of minor:

chills*

muscle aches*

fatigue*

upset stomach*

nausea*

nervous irritability*

*Claims based on traditional homeopathic practice, not accepted medical evidence. Not FDA evaluated.

Warnings:

PREGNANCY OR BREAST FEEDING

If pregnant or breastfeeding, ask a health professional before use.

Do not use if clear seal over the cap is broken or missing.

Keep out of reach of children. In case of overdose, get medical help or contact a Poison Control Center right away.

Stop use and ask a doctor if chills, muscle aches, fatigue, upset stomach, nausea, nervous irritability, or other symptoms do not improve within 7 days or are accompanied by fever.

Directions:

Adults & children ages 12 years and over: Take 5-8 drops under the tongue 3-4 times a day, or as directed by your healthcare professional. Consult a physician for use in children under 12 years of age.

Inactive Ingredients

alcohol (20% by volume), distilled water

Distributed by Apex Energetics. Questions?

16592 Hale Ave., Irvine, CA 92606, USA

PACKAGE LABEL

FUTUREPLEX® B09

ANTITOX®

ACUTE VIROTOX™

Homeopathic Formula

Chills*

Muscle Aches*

Fatigue*

1 fl oz (30 mL)

Alcohol 20% by Volume